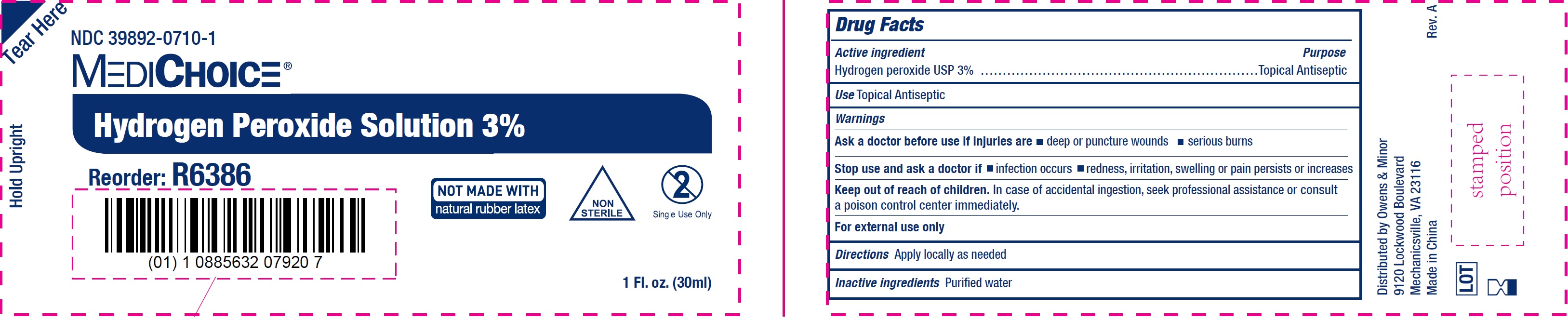 DRUG LABEL: Hydrogen Peroxide
NDC: 39892-0710 | Form: LIQUID
Manufacturer: O&M HALYARD, INC.
Category: otc | Type: HUMAN OTC DRUG LABEL
Date: 20251008

ACTIVE INGREDIENTS: HYDROGEN PEROXIDE 30 mg/1 mL
INACTIVE INGREDIENTS: WATER

Hydrogen Peroxide Solution

Active ingredient

Hydrogen peroxide USP 3%

Purpose

Topical Antiseptic

Use

Topical Antiseptic

Warnings

For external use only

Ask a doctor before use if injuries are

• deep or puncture wounds • serious burns

Stop use and ask a doctor if

• infection occurs • redness, irritation, swelling or pain persists or increases

Keep out of reach of children.

In case of accidental ingestion, seek professional assistance or consult a poison control center immediately.

Directions

Apply locally as needed

Inactive ingredients

Purified water